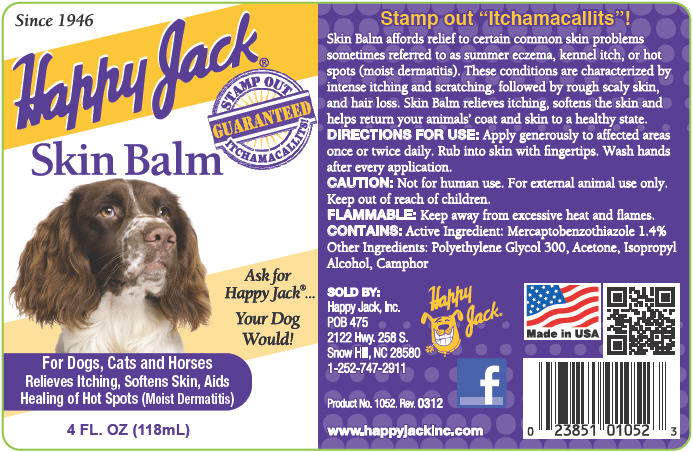 DRUG LABEL: Skin Balm
NDC: 23851-052 | Form: LIQUID
Manufacturer: Happy Jack Inc.
Category: animal | Type: OTC ANIMAL DRUG LABEL
Date: 20240221

ACTIVE INGREDIENTS: 2-mercaptobenzothiazole 14 mg/1 mL
INACTIVE INGREDIENTS: acetone; isopropyl alcohol; camphor (natural); polyethylene glycol 300

Happy Jack®
Skin Balm

Stamp out "Itchamacallits"!

VETERINARY INDICATIONS

Skin Balm affords relief to certain common skin problems sometimes referred to as summer eczema, kennel itch, or hot spots (moist dermatitis). These conditions are characterized by intense itching and scratching, followed by rough scaly skin, and hair loss. Skin Balm relieves itching, softens the skin and helps return your animals' coat and skin to a healthy state.

DIRECTIONS FOR USE

Apply generously to affected areas once or twice daily. Rub into skin with fingertips. Wash hands after every application.

CAUTION

Not for human use. For external animal use only. Keep out of reach of children.

FLAMMABLE

Keep away from excessive heat and flames.

CONTAINS

Active Ingredient

Mercaptobenzothiazole 1.4%

Other Ingredients

Polyethylene Glycol 300, Acetone, Isopropyl Alcohol, Camphor

SOLD BY:
Happy Jack, Inc.
POB 475
2122 Hwy. 258 S.
Snow Hill, NC 28580
1-252-747-2911

Made in USA

Product No. 1052. Rev. 0312

www.happyjackinc.com

PRINCIPAL DISPLAY PANEL - 118 mL Bottle Label

Since 1946

Happy Jack®

STAMP OUT
GUARANTEED
ITCHAMACALLITS!

Skin Balm

Ask for
Happy Jack®...

Your Dog
Would!

For Dogs, Cats and Horses
Relieves Itching, Softens Skin, Aids
Healing of Hot Spots (Moist Dermatitis)

4 FL. OZ (118mL)